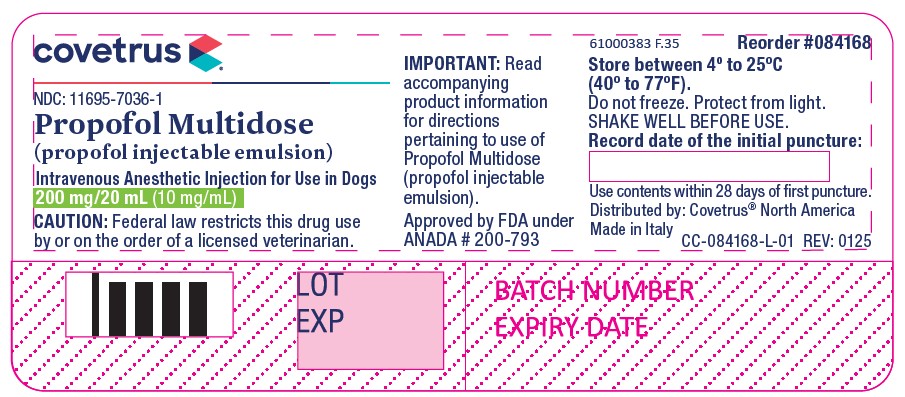 DRUG LABEL: Propofol Multidose
NDC: 11695-7036 | Form: INJECTION, EMULSION
Manufacturer: Covetrus North America
Category: animal | Type: PRESCRIPTION ANIMAL DRUG LABEL
Date: 20250501

ACTIVE INGREDIENTS: PROPOFOL 10 mg/1 mL
INACTIVE INGREDIENTS: SOYBEAN OIL 100 mg/1 mL; GLYCERIN 22.5 mg/1 mL; BENZYL ALCOHOL 20 mg/1 mL; OLEIC ACID 0.6 mg/1 mL; EGG PHOSPHOLIPIDS 12 mg/1 mL; SODIUM HYDROXIDE; NITROGEN; WATER

Propofol Multidose

For Animal Use Only

Propofol Multidose
(propofol injectable emulsion)
Intravenous Anesthetic Injection for Use in Dogs.

CAUTION:

Federal law restricts this drug to use by or on the order of a licensed veterinarian.

DESCRIPTION:

Propofol Multidose is a sterile, nonpyrogenic emulsion containing 10 mg/mL of propofol in a multidose vial for intravenous administration. Each mL contains 10 mg propofol. Propofol is chemically described as 2, 6-diisopropylphenol and has a molecular weight of 178.27. Propofol is very slightly soluble in water and is therefore formulated as a white, oil-in-water emulsion. In addition to the active component, propofol, the formulation also contains soybean oil (100 mg/mL), glycerol (22.5 mg/mL), benzyl alcohol (20 mg/mL), oleic acid (0.6 mg/mL), and egg lecithin (12 mg/mL), with sodium hydroxide to adjust the pH. The Propofol Multidose emulsion is isotonic and has a pH of 6.0 to 8.5.

INDICATIONS:

Propofol Multidose is an anesthetic injection for use in dogs as follows:
For induction of anesthesia.
For maintenance of general anesthesia by intermittent bolus injections for short procedures.
For induction of general anesthesia where maintenance is provided by inhalant anesthetics.

DOSAGE AND ADMINISTRATION:

Administer by intravenous injection only. Shake the vial thoroughly before opening. Propofol is a white stable emulsion; do not use if there is evidence of separation of the phases. Do not use if there is evidence of excessive creaming or aggregation, if large droplets are visible, or if there are other forms of phase separation indicating that the stability of the product has been compromised. Slight creaming, which should disappear after shaking, may be visible upon prolonged standing. Do not use if particulate matter and discoloration are present. Strict aseptic techniques must always be maintained during handling. Failure to follow aseptic handling procedures may result in microbial contamination causing fever, infection/sepsis, and/or other life threatening illness. Do not use if contamination is suspected.
Once a vial is opened, the contents begin a 28-day shelf life. The opened vial should be labeled with “Date Opened” and “Use By” in the space provided. To avoid microbial overgrowth, the contents must be used within 28 days (4 weeks) of the date opened. The opened vial should be placed in a covered container, held at room temperature and used within the allotted 28 day timeframe. Refrigeration is not recommended. Any unused propofol remaining at the end of 28 days should be discarded. The emulsion should not be mixed with other therapeutic agents prior to administration. No specific preanesthetic is either indicated or contraindicated with propofol. The necessity for, choice of, as well as any necessary reduction of dose for the preanesthetic, is left to the discretion of the veterinarian. The dose of propofol is not affected by anticholinergic premedication.

INDUCTION OF GENERAL ANESTHESIA:

For induction, Propofol Multidose should be titrated against the response of the patient over 60 to 90 seconds or until clinical signs show the onset of anesthesia. Rapid injection of propofol (≤5 seconds) may be associated with an increased incidence of apnea^1. The average preserved propofol injectable emulsion induction dose rates for healthy dogs given propofol alone, or when propofol is preceded by a preanesthetic, are indicated in the table below. This table is based on field study results and is for guidance only. The dose and rate for propofol should be based upon patient response.

Induction Dosage Guidelines
Preanesthetic* | Propofol Induction Dose | Propofol Rate of Administration
 | mg/kg | Seconds | mg/kg/min | mL/kg/min
None | 7.6 | 60 to 90 | 5.0 to 7.6 | 0.50 to 0.76
Benzodiazepine/Opioid | 4.7 | 60 to 90 | 3.1 to 4.7 | 0.31 to 0.47
Phenothiazine/Opioid | 4.0 | 60 to 90 | 2.7 to 4.0 | 0.27 to 0.40
Alpha2-agonist/Opioid | 3.2 | 60 to 90 | 2.1 to 3.2 | 0.21 to 0.32

*Doses for preanesthetics may be lower than the label directions for their use as a single medication^2.

The use of preanesthetics markedly reduces propofol requirements. Induction dose sparing was approximately 38% with benzodiazepine/opioid preanesthesia, 47% when dogs were preanesthetized with phenothiazine/opioid, and 58% when dogs were preanesthetized with alpha2-agonist. As with other sedative hypnotic agents, the amount of opioid and/or alpha2-agonist premedication will influence the response of the patient to an induction dose of propofol. In the presence of preanesthesia, the dose of propofol may be reduced with increasing age of the animal. The dose of propofol should always be titrated against the response of the patient. During induction, additional low doses of propofol, similar to those used for maintenance with propofol, may be administered to facilitate intubation or the transition to inhalant maintenance anesthesia.

MAINTENANCE OF GENERAL ANESTHESIA:

A. Intermittent Propofol Injections:
Anesthesia can be maintained by administering Propofol Multidose in intermittent IV injections. Clinical response will be determined by the amount and the frequency of maintenance injections. The following table is based on field study results and is provided for guidance:

Maintenance Dosage Guidelines
Preanesthetic* | Propofol Maintenance Dose | Propofol Rate of Administration
 | mg/kg | Seconds | mg/kg/min | ml/kg/min
None | 3.2 | 60 | 3.2 | 0.32
Benzodiazepine/Opioid | 1.7 | 60 | 1.7 | 0.17
Phenothiazine/Opioid | 2.0 | 60 | 2.0 | 0.20

*Doses for preanesthetics may be lower than the label directions for their use as a single medication^2.

Maintenance dose sparing was approximately 48% with benzodiazepine/opioid preanesthesia and 37% when dogs were preanesthetized with phenothiazine/opioid. Repeated maintenance doses of propofol do not result in increased recovery times or dosing intervals, indicating that the anesthetic effects of propofol are not cumulative.
B. Maintenance by Inhalant Anesthetics:
Due to the rapid metabolism of propofol, additional low doses of propofol, similar to those used for maintenance with propofol, may be required to complete the transition to inhalant maintenance anesthesia. Clinical trials using propofol have shown that it may be necessary to use a higher initial concentration of the inhalant anesthetic halothane than is usually required following induction using barbiturate anesthetics, due to rapid
recovery from propofol^3.

CONTRAINDICATIONS:

Propofol Multidose is contraindicated in dogs with a known hypersensitivity to propofol or its components, or when general anesthesia or sedation are contraindicated.

WARNINGS:

Rapid bolus administration (induction or maintenance) or accidental overdosage of propofol may cause undesirable cardiorespiratory depression including hypotension and oxygen desaturation. Respiratory arrest (apnea) could occur. In cases of respiratory depression, stop drug administration, establish a patent airway, and initiate assisted or controlled ventilation with pure oxygen. Cardiovascular depression should be treated with plasma expanders, pressor agents, antiarrhythmic agents or other techniques as appropriate for the observed abnormality.

When using propofol, dogs should be continuously monitored and facilities for the maintenance of a patent airway, artificial ventilation, and oxygen supplementation must be immediately available.

HUMAN WARNINGS:

Not for use in humans. Keep out of the reach of children.
Rare cases of self-administration have been reported, including fatalities. Propofol Multidose should be managed to prevent the risk of diversion, through such measures as restriction of access and the use of drug accountability procedures appropriate to the clinical setting. Exercise caution to avoid accidental self-injection. Overdose is likely to cause cardiorespiratory depression (such as hypotension, bradycardia and/or apnea). Remove the individual from the source of exposure and seek medical attention. Respiratory depression should be treated by artificial ventilation and oxygen. Hypersensitivity reactions to propofol, including anaphylaxis, may occur in some individuals who are also allergic to muscle relaxants^4. Avoid inhalation and direct contact of this product with skin, eyes, and clothes. In case of contact, eyes and skin should be liberally flushed with water for 15 minutes. Consult a physician if irritation persists.

CONTACT INFORMATION:

To report suspected adverse drug events, for technical assistance or to obtain a copy of the Safety Data Sheet, contact Covetrus® North America at (855) 724-3461 or covetrus.com. For additional information about adverse drug experience reporting for animal drugs, contact FDA at 1-888-FDA-VETS or online at www.fda.gov/reportanimalae.

PRECAUTIONS:

1. Anesthesia effects: Careful monitoring of the patient is necessary when using propofol as a maintenance anesthetic due to the possibility of rapid arousal. Apnea may occur following maintenance doses of propofol. Following induction, additional propofol may be needed to complete the transition to inhalant maintenance anesthesia due to rapid recovery from propofol. Doses administered during the transition to inhalant anesthesia may result in apnea. Propofol has also been used during inhalant maintenance anesthesia to increase anesthetic depth. Propofol used during inhalant maintenance may result in apnea.

2. Physiological effects: Mild hypotension may occur during propofol anesthesia.

3. Preanesthetics: Preanesthetics may increase the anesthesia or sedative effect of propofol and result in more pronounced changes in systolic, diastolic and mean arterial blood pressures.

4. Alpha2-agonists: Propofol Multidose for maintenance anesthesia was not evaluated in the presence of alpha2-agonist preanesthesia. The use of an alpha2-agonist as a preanesthetic may significantly reduce the amount of propofol induction and maintenance anesthetic requirements. Careful patient monitoring during anesthetic induction and maintenance is necessary to avoid anesthetic overdose.

5. Breeding animals: The use of propofol in pregnant and breeding dogs has not been evaluated. Propofol crosses the placenta and, as with other general anesthetic agents, the administration of propofol may be associated with neonatal depression.

6. Neonates and pups: Propofol has not been evaluated in dogs less than 10 weeks of age.

7. Compromised or debilitated dogs: Doses may need adjustment for geriatric or debilitated patients. The administration of propofol to patients with renal failure and/or hepatic failure has not been evaluated. As with other anesthetic agents, caution should be exercised in dogs with cardiac, respiratory, renal or hepatic impairment, or in hypovolemic or debilitated dogs. Geriatric dogs may require less propofol for induction of anesthesia (see Dosage and Administration).

8. Sighthounds: Propofol induction and maintenance produced satisfactory anesthesia and recoveries in sighthounds. In the clinical study, a total of 27 sighthounds were induced with propofol, 6 of which were maintained on propofol. Induction doses were similar in sighthounds compared to other animals, however, recoveries were delayed.

9. Cardiac arrhythmias: In one study, propofol increased myocardial sensitivity to the development of epinephrine induced ventricular arrhythmias in a manner similar to other anesthetics^5. In the unpreserved propofol injectable emulsion field study, transient ventricular arrhythmias associated with propofol were observed in 2 of 145 animals induced and maintained on propofol.

10. Concurrent medication: No significant adverse interactions with commonly used drugs have been observed.

11. Perivascular administration: Perivascular administration does not produce local tissue reaction.

12. Aseptic Handling: Propofol Multidose contains benzyl alcohol as a bacteriostatic preservative. Aseptic technique during handling is recommended. Use of vial contents beyond 28 days may result in microbial contamination causing fever, infection/sepsis, and/or other lifethreatening illness. Do not use if contamination is suspected.

13. Cats: Propofol Multidose contains benzyl alcohol which may be toxic to cats.

ADVERSE REACTIONS:

The primary side effect of propofol is respiratory depression as evidenced by tachypnea and apnea. Other less frequent adverse reactions include:
Respiratory: labored breathing
Cardiovascular: hypotension, hypertension, bradycardia, tachycardia, membrane cyanosis, arrhythmias
Musculoskeletal: fasciculations, tenseness, paddling, movements
Central Nervous System: excitation, opisthotonos, seizures, excessive depression
Gastrointestinal: emesis, retching, salivation.

CLINICAL PHARMACOLOGY:

Propofol Multidose (propofol injectable emulsion) is an intravenous sedative hypnotic agent for use in the induction and maintenance of anesthesia. Intravenous injection of propofol in the dog is followed by extensive metabolism of propofol in the liver to inactive conjugates which are excreted in the urine. Elimination from the central compartment occurs rapidly, with an initial elimination phase of less than 10 minutes. Induction of anesthesia will usually be observed within 65 to 120 seconds after the beginning of propofol administration. The duration of anesthesia following the recommended induction doses averages 5.5 to 6.5 minutes in preanesthetized and unpreanesthetized animals. The duration of anesthesia following recommended maintenance doses in unpreanesthetized dogs averages 8.5 minutes. In preanesthetized dogs (phenothiazine/opioid or benzodiazepine/opioid), maintenance anesthesia averages 5.0 to 5.4 minutes after each maintenance dose. Recovery from propofol is rapid; full standing recovery is generally observed within 20 minutes. The use of certain premedicants may result in prolonged recovery. Recovery may be delayed in Sighthounds. Propofol has been used in association with anticholinergics, phenothiazines, alpha2-agonists, opioids, and benzodiazepines, as well as inhalant anesthetics. No pharmacological incompatibility has been observed.

EFFECTIVENESS:

Canine induction/maintenance field study with unpreserved propofol injectable emulsion: Propofol was evaluated in a multisite field study in dogs. Effectiveness was evaluated in 419 client owned dogs of ASA Category I-II, ranging in age between 0.2 and 16 years of age, and in size between 1.3 and 72.6 kg. Dogs admitted to veterinary clinics for various procedures requiring surgical or nonsurgical procedures were assigned to 1 of 10 treatment groups according to the patient needs (see table below). Groups 1, 2, 8, 9 and 10 received propofol as maintenance anesthetic for short procedures of ≤ 20 minutes. Groups 3, 4, 5, 5A, 6 and 7 received an inhalant maintenance anesthetic for procedures generally > 20 minutes. Procedures included ovariohysterectomy, castration, dental, radiography, endoscopy, biopsy, gastroscopy and mass removal.

Treatment Group | Preanesthetic | Induction | Maintenance | No. Dogs
1 | None | Propofol | Propofol | 49
2 | Phenothiazine | Propofol | Propofol | 48
3 | None | Propofol | Inhalant | 52
4 | Phenothiazine/Opioid | Propofol | Inhalant | 54
5 | Alpha2-agonist/Opioid | Propofol | Inhalant | 46
5A | Benzodiazepine/Opioid | Propofol | Inhalant | 13
6 | Benzodiazepine/Opioid | Propofol | Inhalant | 53
7 | Phenothiazine/Opioid | Propofol | Inhalant | 56
8 | Phenothiazine/Opioid | Propofol | Propofol | 16
9 | Alpha2-agonist/Opioid | Propofol | Propofol | 16
10 | Benzodiazepine/Opioid | Propofol | Propofol | 16

Doses of propofol required for induction were markedly reduced by the presence of preanesthesia. The mean duration of anesthesia following propofol induction ranged from 5.7 to 10.4 minutes among the treatment groups. The mean duration of anesthesia following administration of propofol maintenance doses ranged between 2.96 to 6.51 minutes, and was longer in the presence of preanesthesia than with propofol alone.
Heart rate, blood pressure, respiratory rate, hemoglobin oxygen saturation and rectal temperature were measured throughout anesthesia. The most common adverse reactions involved the respiratory system. Tachypnea and apnea were observed in 180 and 110 dogs, respectively. Apnea occurred most often during the interval immediately following induction with propofol (0 to 5 minutes post intubation) and varied in duration from a few seconds to several minutes. All dogs responded to treatment. Other less frequent adverse reactions included hypertension, tachycardia, cyanosis, cardiac arrhythmias, muscle fasciculations, paddling, excitation and vomiting.

Canine induction/maintenance field study with multidose preserved propofol injectable emulsion: Preserved propofol injectable emulsion was evaluated in a multi-site field study in dogs. Effectiveness was evaluated in 138 client-owned dogs of ASA Category I to II ranging in age between 0.25 to 17 years of age, and in size between 1.8 and 51.5 kg. Dogs were assessed for various surgical and nonsurgical procedures and assigned to one of six treatment groups according to the patient needs (see table below). Groups 1 to 3 included dogs requiring general anesthesia for procedures ≤ 20 minutes that were maintained using propofol. Dogs in groups 4 to 6 had procedures ≥ 20 minutes and received an inhalant for maintenance anesthesia. Procedures included castration, dental, mass removal, radiographs and ovariohysterectomy.

Treatment Group | Preanesthetic | Induction | Maintenance | No. Dogs
1 | None | Propofol | Propofol | 23
2 | Benzodiazepine/Opioid | Propofol | Propofol | 25
3 | Phenothiazine/Opioid | Propofol | Propofol | 25
4 | Benzodiazepine/Opioid | Propofol | Inhalant | 22
5 | Phenothiazine/Opioid | Propofol | Inhalant | 22
6 | Alpha2-agonist/Opioid | Propofol | Inhalant | 21

Doses of preserved propofol injectable emulsion required for induction were markedly reduced by the presence of preanesthetics. The mean duration of anesthesia following propofol induction ranged from 5.8 to 6.5 minutes among treatment groups. The mean duration of anesthesia following administration of propofol maintenance doses ranged from 5.0 to 8.0 minutes. The mean time from extubation to standing recovery among groups maintained on preserved propofol injectable emulsion ranged from 6.4 to 13.7 minutes. Heart rate, blood pressure, respiratory rate, end-tidal CO2, hemoglobin oxygen saturation and rectal temperature were measured throughout anesthesia. The most commonly observed adverse reaction was apnea. Tachypnea and apnea were observed in 15 and 21 dogs, respectively. All cases of apnea resumed normal breathing spontaneously, or responded satisfactorily to oxygen supplementation and/or controlled ventilation. Hypotension and bradycardia also occurred in association with maintenance anesthesia. Other less frequent adverse reactions included hypertension, bradycardia, excitation, cyanosis, cardiac arrhythmias, muscle fasciculations, paddling, tachycardia and vomiting.

Field study results and adverse reactions were similar between the unpreserved propofol injectable emulsion and multidose preserved propofol injectable emulsion.

Preserved propofol injectable emulsion was used safely in dogs that received steroids, heartworm preventative, and flea preventative products.

ANIMAL SAFETY:

Unpreserved propofol injectable emulsion safety study: Two propofol groups received total doses of either 11.6 (lower dose) or 29.7 mg/kg (higher dose) during each anesthetic episode. In group 1, anesthesia was induced with 6.5 mg/kg and maintained with 3 bolus injections of 1.7 mg/kg propofol. Group 2 dogs received 19.5 mg/kg propofol for induction and 6 bolus injections of 1.7 mg/kg propofol for maintenance. A third group of dogs was injected with saline (controls) at a volume equal to that administered to the higher dose dogs. Each group included a total of 8 Beagles (4 males: 4 females). Dogs were anesthetized 6 times over 11 days (every other day).

Recovery times were much longer in higher dose group dogs, except for the first episode of anesthesia in which there was a small difference between the doses. The time to recovery increased after the first anesthetic episode. Average daily heart rate tended to increase over time in dogs that received propofol, but was within the normal range for Beagles.

During anesthesia in the lower propofol dose group, transient increases in respiratory rate occurred 1 minute after induction and declined to baseline within 5 minutes. Respiratory rate declined initially in response to the higher propofol dose, then returned to or above baseline within 10 minutes. Heart rate increased after induction in both dose groups and gradually returned to baseline. Transient, clinically acceptable increases in systolic and mean blood pressure and decreases in diastolic blood pressure (higher dose only), occurred immediately (by 1 minute) after propofol administration in both groups.

The duration of apnea averaged 28 and 70 seconds after induction doses of 6.5 and 19.5 mg/kg, respectively, and did not increase with repeated episodes of propofol anesthesia. All animals which became apneic resumed breathing spontaneously; at no time in the study was oxygen supplementation or assisted ventilation administered.

Tachypnea, another adverse reaction, was transient and clinically manageable; its incidence was similar among the lower and higher dose groups. Muscle fasciculations were observed during maintenance with intermittent bolus injections and were considered to be related to a light plane of anesthesia. Changes in mucous membrane color were consistent with mild respiratory depression and subsequent vasodilation. Mucous membrane color was normal in all dogs within 5 minutes of induction.

Hematology and clinical chemistry findings were not attributed to the administration of propofol.

Preanesthetics: Propofol is compatible with benzodiazepines, opioids, alpha2-agonists, and phenothiazines as commonly used for preanesthesia in surgical practice.

Inhalant Anesthetics: Propofol is compatible with commonly used inhalant anesthetics.

STORAGE INFORMATION:

Propofol undergoes oxidative degradation in the presence of oxygen and is therefore packaged under nitrogen to eliminate this degradation path. Store between 4° to 25°C (40° to 77°F). Do not freeze. Protect from light.

Shake well before use.

Use contents within 28 days of first puncture.

HOW SUPPLIED:

Propofol Multidose is supplied in cartons of five-20 mL (200 mg per vial) vials containing 10 mg propofol per mL.

REFERENCES:

1. Smith, J.A., J.S. Gaynor. R.M. Bednarski and W.W. Muir. Adverse effects of administration of propofol with various preanesthetic regimens in dogs. JAVMA. 202:1111-1115 (1993).
2. Plumb, D.C. ed. Veterinary Drug Handbook, Second Edition. Iowa State University Press, Ames, IA (1995).
3. Muir, W.W., J.A.E. Hubbell, R.T. Skarda, and R.M. Bednarski. Handbook of Veterinary Medicine, Second Edition. Mosby-Year Book, Inc. (1995).
4. Laxenaire. M.C., E. Mata-Bermejo, D.A. Moneret-Vaurrin and J.L. Gueant. Life-threatening anaphylactoid reactions to propofol (Diprivan®). Anesthesiology 77:275-280 (1992).5. Kamibayashi. T., Y. Hayashi, K. Sumikawa, A. Yamatodani, K. Kawabata and I. Yoshiya. Enhancement by propofol of epinephrine-induced arrhythmias in dogs. Anesthesiology 75:1035-1040 (1991).

Approved by FDA under ANADA # 200-793

Distributed by:
Covetrus® North America
400 Metro Place North
Dublin, OH 43017

covetrus.com

Made in Italy
CC-084168-C-01 REV: 0125

PRINCIPAL DISPLAY PANEL 200 MG / 20 ML Label

Image of 20 mL Label